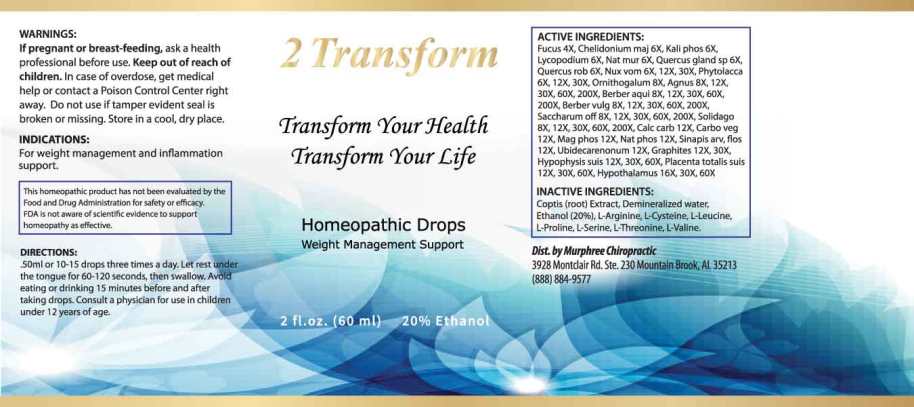 DRUG LABEL: 2 Transform
NDC: 81403-0001 | Form: LIQUID
Manufacturer: Murphree Chiropractic
Category: homeopathic | Type: HUMAN OTC DRUG LABEL
Date: 20260112

ACTIVE INGREDIENTS: FUCUS VESICULOSUS 4 [hp_X]/1 mL; CHELIDONIUM MAJUS WHOLE 6 [hp_X]/1 mL; DIBASIC POTASSIUM PHOSPHATE 6 [hp_X]/1 mL; LYCOPODIUM CLAVATUM SPORE 6 [hp_X]/1 mL; SODIUM CHLORIDE 6 [hp_X]/1 mL; QUERCUS ROBUR NUT 6 [hp_X]/1 mL; QUERCUS ROBUR TWIG BARK 6 [hp_X]/1 mL; STRYCHNOS NUX-VOMICA SEED 6 [hp_X]/1 mL; PHYTOLACCA AMERICANA ROOT 6 [hp_X]/1 mL; ORNITHOGALUM UMBELLATUM WHOLE 8 [hp_X]/1 mL; CHASTE TREE FRUIT 8 [hp_X]/1 mL; BERBERIS AQUIFOLIUM ROOT BARK 8 [hp_X]/1 mL; BERBERIS VULGARIS ROOT BARK 8 [hp_X]/1 mL; SUCROSE 8 [hp_X]/1 mL; SOLIDAGO VIRGAUREA FLOWERING TOP 8 [hp_X]/1 mL; OYSTER SHELL CALCIUM CARBONATE, CRUDE 12 [hp_X]/1 mL; ACTIVATED CHARCOAL 12 [hp_X]/1 mL; MAGNESIUM PHOSPHATE, DIBASIC TRIHYDRATE 12 [hp_X]/1 mL; SODIUM PHOSPHATE, DIBASIC, HEPTAHYDRATE 12 [hp_X]/1 mL; SINAPIS ARVENSIS FLOWERING/FRUITING TOP 12 [hp_X]/1 mL; UBIDECARENONE 12 [hp_X]/1 mL; GRAPHITE 12 [hp_X]/1 mL; SUS SCROFA PITUITARY GLAND 12 [hp_X]/1 mL; SUS SCROFA PLACENTA 12 [hp_X]/1 mL; BOS TAURUS HYPOTHALAMUS 16 [hp_X]/1 mL
INACTIVE INGREDIENTS: COPTIS CHINENSIS ROOT; ARGININE; CYSTEINE; LEUCINE; PROLINE; SERINE; THREONINE; VALINE; WATER; ALCOHOL

DRUG FACTS:

ACTIVE INGREDIENTS:

Fucus Vesiculosus 4X, Chelidonium Majus 6X, Kali Phosphoricum 6X, Lycopodium Clavatum 6X, Natrum Muriaticum 6X, Quercus Glandium Spiritus 6X, Quercus Robur 6X, Nux Vomica 6X, 12X, 30X, Phytolacca Decandra 6X, 12X, 30X, Ornithogalum Umbellatum 8X, Agnus Castus 8X, 12X, 30X, 60X, 200X, Berberis Aquifolium 8X, 12X, 30X, 60X, 200X, Berberis Vulgaris 8X, 12X, 30X, 60X, 200X, Saccharum Officinale 8X, 12X, 30X, 60X, 200X, Solidago Virgaurea 8X, 12X, 30X, 60X, 200X, Calcarea Carbonica 12X, Carbo Vegetabilis 12X, Magnesia Phosphorica 12X, Natrum Phosphoricum 12X, Sinapis Arvensis, Flos 12X, Ubidecarenonum 12X, Graphites 12X, 30X, Hypophysis Suis 12X, 30X, 60X, Placenta Totalis Suis 12X, 30X, 60X, Hypothalamus (Bovine) 16X, 30X, 60X.

INDICATIONS:

For weight management and inflammation support.

This homeopathic product has not been evaluated by the Food and Drug Administration for safety or efficacy. FDA is not aware of scientific evidence to support homeopathy as effective.

WARNINGS:

If pregnant or breast-feeding, ask a health professional before use.

Keep out of reach of children. In case of overdose, get medical help or contact a Poison Control Center right away.

Do not use if tamper evident seal is broken or missing. Store in a cool, dry place.

Keep out of reach of children. In case of overdose, get medical help or contact a Poison Control Center right away.

DIRECTIONS:

.50ml or 15 drops three times a day. Let rest under the tongue for 60-120 seconds, then swallow. Avoid eating or drinking 15 minutes before and after taking drops. Consult a physician for use in children under 12 years of age.

INDICATIONS:

For weight management and inflammation support.

This homeopathic product has not been evaluated by the Food and Drug Administration for safety or efficacy. FDA is not aware of scientific evidence to support homeopathy as effective.

INACTIVE INGREDIENTS:

Coptis (Root) Extract, Demineralized water, Ethanol (20%), L-Arginine, L-Cysteine, L-Leucine, L-Proline, L-Serine, L-Threonine, L-Valine.

QUESTIONS:

Dist. by: Murphree Chiropractic

3928 Montclair Rd. Ste, 230

Mountain Brook, Al 35213

(888) 884-9577

PACKAGE LABEL DISPLAY:

2 Transform

Transform Your Health

Transform Your Life

Homeopathic Drops

Weight Management

Support

2 fl.oz. (60 ml)